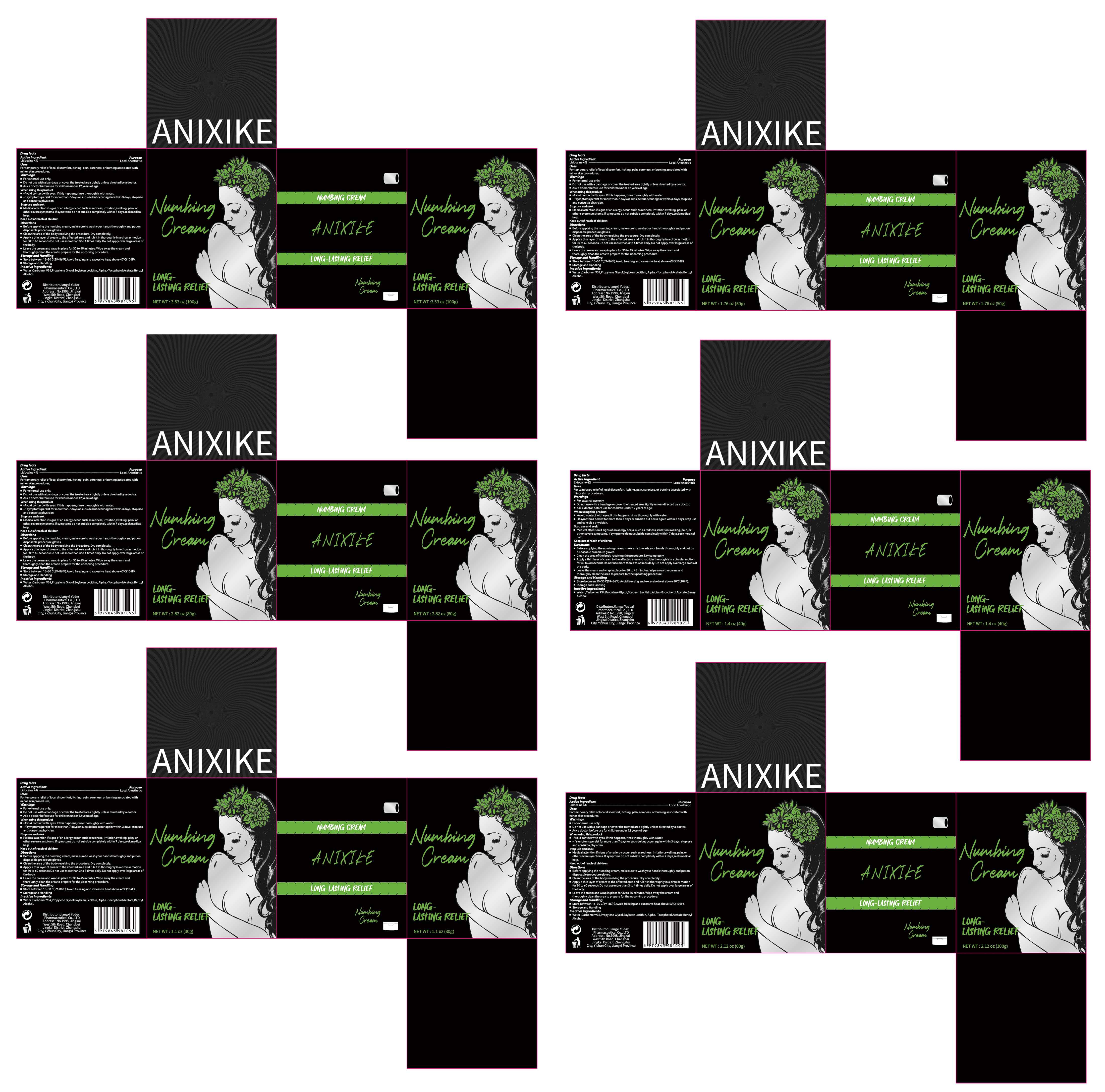 DRUG LABEL: ANIXIKE Numbing
NDC: 85248-088 | Form: CREAM
Manufacturer: Jiangxi Yudexi Pharmaceutical Co., LTD
Category: otc | Type: HUMAN OTC DRUG LABEL
Date: 20260207

ACTIVE INGREDIENTS: LIDOCAINE 4 g/100 g
INACTIVE INGREDIENTS: .ALPHA.-TOCOPHEROL ACETATE; BENZYL ALCOHOL; PROPYLENE GLYCOL; SOYBEAN LECITHIN; WATER; CARBOMER 934

85248-088

Active Ingredient

Lidocaine 4%

Purpose

Local Anesthetic

Use

For temporary relief of local discomfort, itching, pain, soreness,or burning associated with minor skin procedure

Warnings

■For external use only. ■Do not use with a bandage or cover the treated area tightly unless directed by a doctor。 ■ Ask a doctor before use for children under 12 years of age.

■Do not use with a bandage or cover the treated area tightly unless directed by a doctor

When Using

■Avoid contact with eyes, If this happens, rinse thoroughly with water. ■ -If symptoms persist for more than 7 days or subside but occur again within 3 days, stop useand consult a physician.

Stop Use

■Meditcal attention if signs of an alerqy occur,such as rednes,irtation,sweling, pain, or other severe symptoms.If symptoms do not subside completely within 7 days, seek medical help.

Ask Doctor

■Meditcal attention if signs of an alerqy occur,such as rednes,irtation,sweling, pain, or other severe symptoms.If symptoms do not subside completely within 7 days, seek medical help. ■ Ask a doctor before use for children under 12 years of age. ■ -If symptoms persist for more than 7 days or subside but occur again within 3 days, stop useand consult a physician.

Keep Oot Of Reach Of Children

Keep out of reach of children

Directions

■Before applying the numbing cream,make sure to wash your hands thoroughly and put ondisposable procedure gloves.
■Clean the area of the body receivina the procedure. Dry completely
■Apply athin layer of cream to the affected area and rub it in thoroughly in a circular motionfor 30 to 60 seconds.Do not use more than 3 to 4 times daily. Do not apply over large areas of
the body.
■Leave the cream and wrap in place for 30 to 45 minutes,Wipe away the cream and thoroughly clean the area to prepare for the upcoming procedure.

Other information

■Store between 15-30 C(59-86°F).Avoid freezing and excessive heat above 40°C(104F) ■Storage and Handling

Inactive ingredients

■Water ,Carbomer 934,Propylene Glycol,Soybean Lecithin,.Alpha.-Tocopherol Acetate,Benzyl Alcohol.